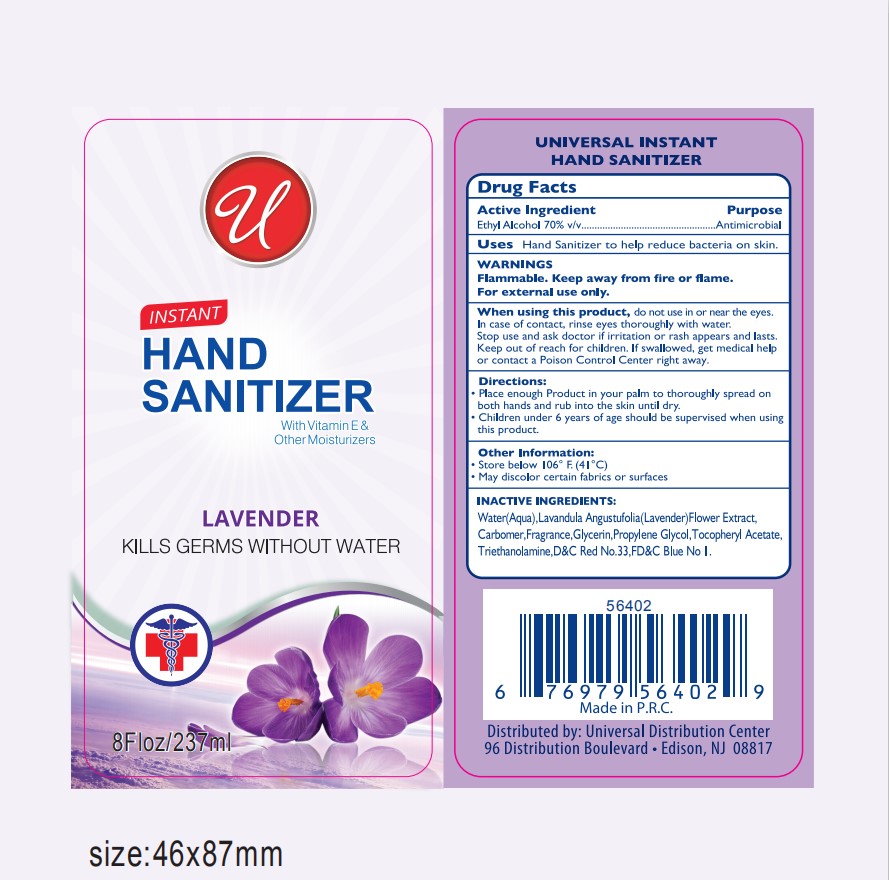 DRUG LABEL: Instant Hand Sanitizer Lavender
NDC: 76114-006 | Form: SOLUTION
Manufacturer: Zhejiang Aidi Cosmetics Co., Ltd
Category: otc | Type: HUMAN OTC DRUG LABEL
Date: 20200424

ACTIVE INGREDIENTS: ALCOHOL 70 mL/100 mL
INACTIVE INGREDIENTS: GLYCERIN; WATER; CARBOMER 934; PROPYLENE GLYCOL; ALPHA-TOCOPHEROL ACETATE; TRIETHANOLAMINE SULFATE; D&C RED NO. 33; FD&C BLUE NO. 1; LAVANDULA ANGUSTIFOLIA FLOWER

NA

Active Ingredient(s)

Ethyl Alcohol 70% v/v

Purpose

Antimicrobial

Use

Hand sanitizer to help reduce bacteria on the skin

Warnings

Flammable. Keep away from fire or flame

For external use only.

When using this product do not use in or near the eyes. In case of contact with eyes, rinse eyes thoroughly with water.

Stop use and ask a doctor if irritation or rash appears and lasts

Keep out of reach of children. If swallowed, get medical help or contact a Poison Control Center right away.

Directions

Place enough product in your palm to thoroughly spread on both hands and rub into the skin untill dry

Children under 6 years of age shoud be supervised when using this

Other information

Do not store above 106F (41C)

May discolor certain fabrics or surfaces

Inactive ingredients

Water, lavandula angustufolia (lavender) flower extract, carbomer, fragrance, propylene glycol, glycerin, tocopheryl acetate, triethanolamine, DC Red No 33, FD C Blue No 1